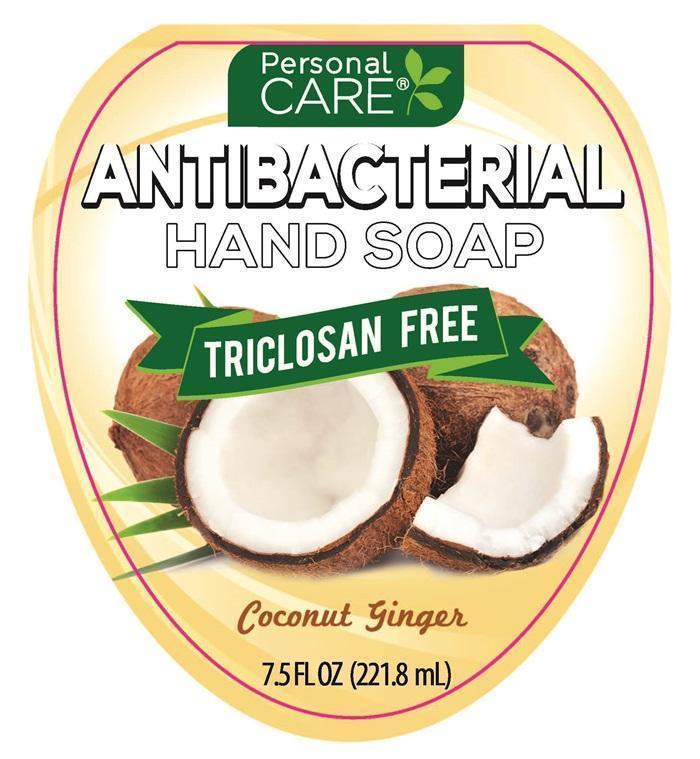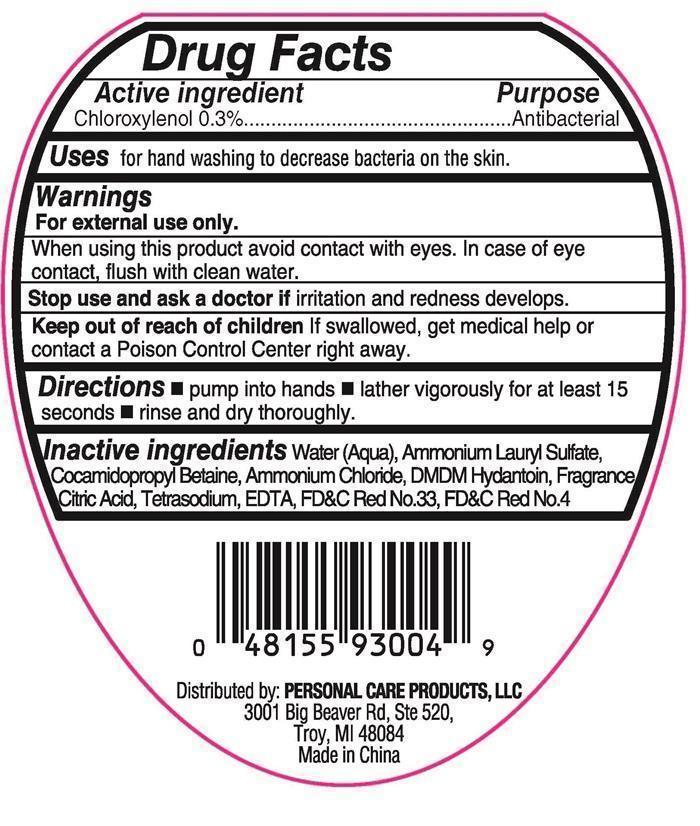 DRUG LABEL: Personal Care Antibacterial Hand
NDC: 29500-9301 | Form: LIQUID
Manufacturer: Personal Care Products, LLC
Category: otc | Type: HUMAN OTC DRUG LABEL
Date: 20150901

ACTIVE INGREDIENTS: CHLOROXYLENOL 0.6657 mg/221.8 mL
INACTIVE INGREDIENTS: AMMONIUM LAURYL SULFATE; COCAMIDOPROPYL BETAINE; AMMONIUM CHLORIDE; DMDM HYDANTOIN; CITRIC ACID MONOHYDRATE; EDETATE SODIUM; D&C RED NO. 33; FD&C RED NO. 4; WATER

Active ingredient

Choroxylenol 0.3 %

Purpose

Antibacterial

Keep out of reach of children.

If swallowed, get medical help or contact a Poison Control Center right away.

Warnings

For external use only.

Uses

for hand washing to decrease bacteria on the skin.

When using this product

avoid contact with eyes. In case of eye contact, flush with clean water.

Stop use and ask a doctor if

irritation and redness developes.

Directions

- pump into hands
- lather vigorously for at least 15 seconds
- rinse and dry thoroughly.

Inactive ingredients

Water (Aqua), Ammonium Lauryl Sulfate, Cocamidopropyl Betaine, Ammonium Chloride, DMDM Hydantoin, Fragrance, Citric Acid, Tetrasodium EDTA, FD and C Red No.33, FD and C Red No.4

Personal CARE® ANTIBACTERIAL HAND SOAP Product Label - Coconut Ginger

Personal CARE® ANTIBACTERIAL HAND SOAP

TRICLOSAN FREE

Coconut Ginger

7.5 FL OZ (221.8 mL)

Distributed by: PERSONAL CARE PRODUCTS, LLC

3001 Big Beaver Rd, Ste 520,

Troy, MI 48084

Made in China